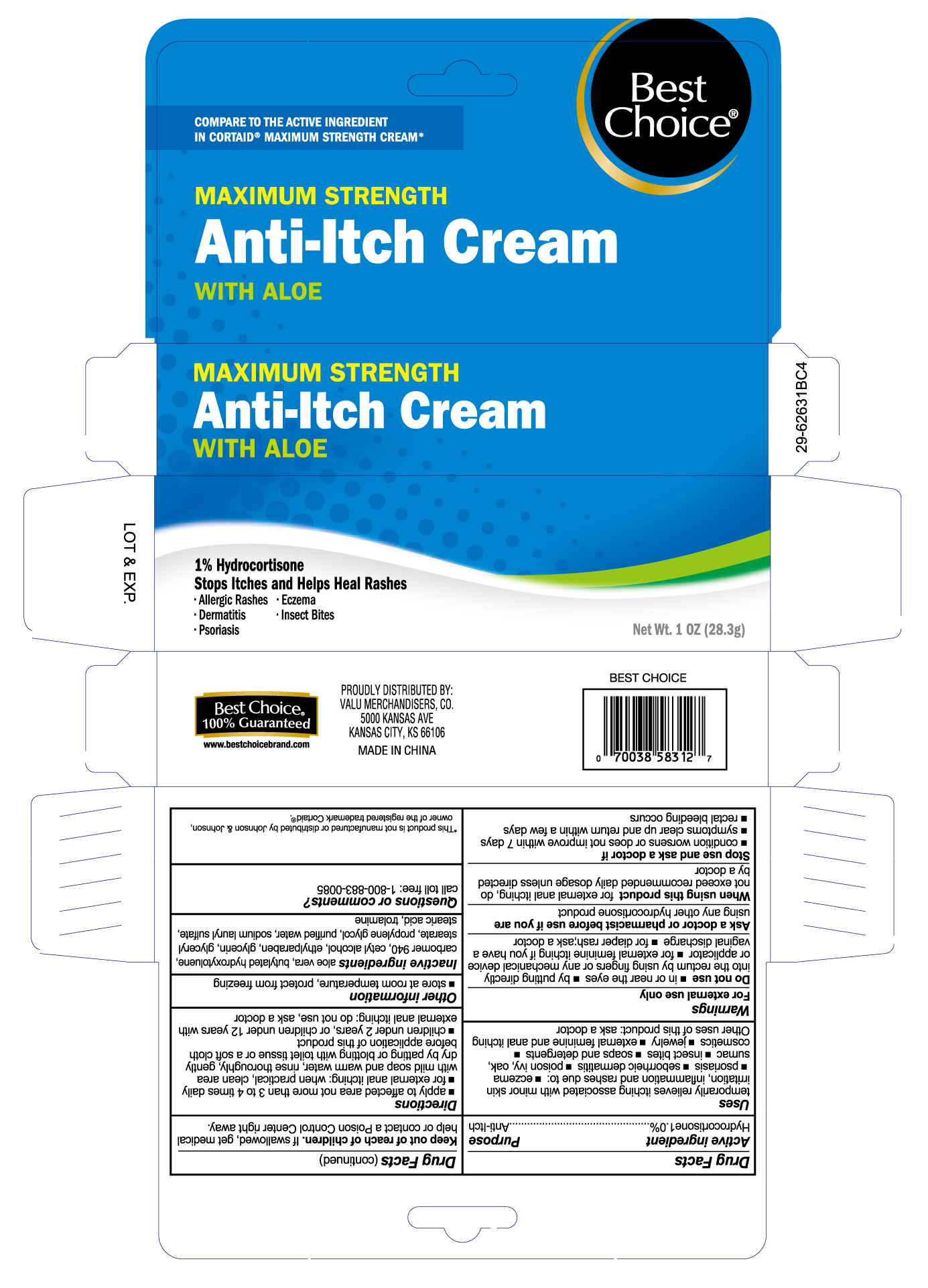 DRUG LABEL: Hydrocortisone
NDC: 63941-312 | Form: CREAM
Manufacturer: Valu Merchandisers, Co.
Category: otc | Type: HUMAN OTC DRUG LABEL
Date: 20230127

ACTIVE INGREDIENTS: HYDROCORTISONE 10 mg/1 g
INACTIVE INGREDIENTS: BUTYLATED HYDROXYTOLUENE; CETYL ALCOHOL; GLYCERIN; GLYCERYL MONOSTEARATE; ISOPROPYL MYRISTATE; METHYLPARABEN; PROPYLPARABEN; WATER; SQUALENE; STEARIC ACID

Best Choice Hydrocortisone

Active Ingredient

Hydrocortisone 1.0%

Purpose

Anti-itch

Uses

temporarily relieves itching associated with minor skin irritation, inflammation and rashes due to:

- eczema

- psoriasis
- seborrheic dermatitis

- poison ivy, oak, sumac

- insect bites

- soaps and detergents

- cosmetics

- jewelry
- external feminine and anal itching

Other uses of this product: ask a doctor

Warnings

For external use only

Do not use

- in or near the eyes
- by putting directly into the rectum by using fingers or any mechanical device or applicator
- for external feminine itching if you have a vaginal discharge
- for diaper rash: ask a doctor.

Ask a doctor or pharmacist before use if you are

using any other hydrocortisone product

When using this product

for external anal itching, do not exceed recommended daily dosage unless directed by a doctor

Stop use and ask a doctor if

- condition worsens or does not improve within 7 days
- symptoms clear up and return within a few days
- rectal bleeding occurs

Keep out of reach of children

If swallowed, get medical help or contact a Poison Control Center right away.

Directions

- apply to affected area not more than 3 to 4 times daily
- for external anal itching: when practical, clean area with mild soap and warm water, rinse thoroughly, gently dry by patting or blotting with toilet tissue or a soft cloth before application of this product
- children under 2 years, or children under 12 years with external anal itching: do not use, ask a doctor

Other information

store at room temperature, protect from freezing

Inactive ingredients

aloe vera, butylated hydroxytoulene, carbomer 940, cetyl alcohol, ethylparaben, glycerin, glyceryl stearate, propylene glycol, purified water, sodium lauryl sulfate, stearic acid, trolamine

Package label

Best Choice Hydrocortisone Anti-Itch Cream